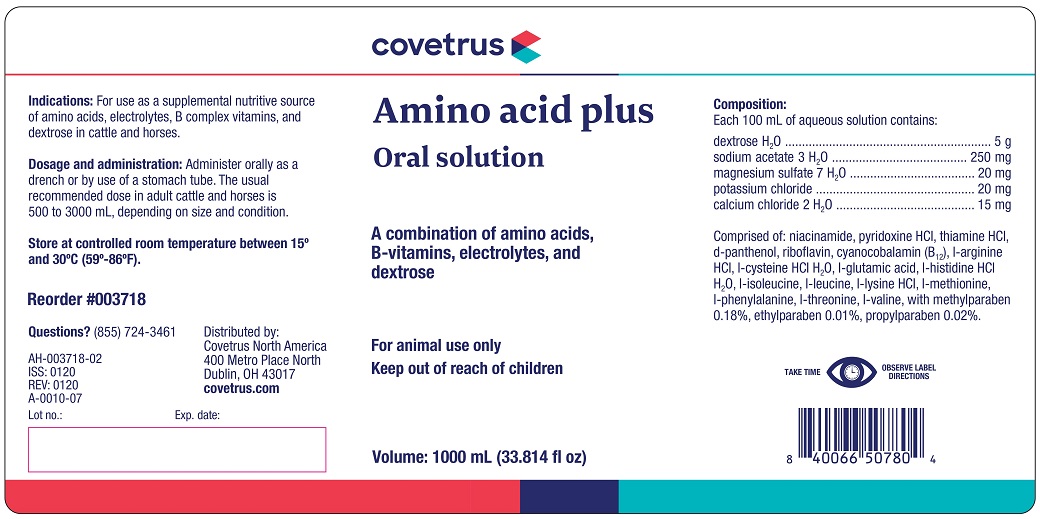 DRUG LABEL: AMINO ACID 
NDC: 11695-4120 | Form: SOLUTION
Manufacturer: Covetrus North America
Category: animal | Type: OTC ANIMAL DRUG LABEL
Date: 20210106

ACTIVE INGREDIENTS: DEXTROSE MONOHYDRATE 5000 mg/100 mL; CALCIUM CHLORIDE ANHYDROUS 15 mg/100 mL; MAGNESIUM SULFATE HEPTAHYDRATE 20  mg/100 mL; POTASSIUM CHLORIDE 20 mg/100 mL; SODIUM ACETATE ANHYDROUS 250 mg/100 mL
INACTIVE INGREDIENTS: VALINE

Amino acid plus

INDICATIONS AND USAGE

A combination of amino acids, B-vitamins, electrolytes and dextrose

For animl use only

Keep out of reach of children

Indications

For use as a supplemental nutritive source of amino acids, electrolytes, B complex vitamins, and dextrose for cattle and horses.

Dosage and administration

Administer orally as a drench or by use of a stomach tube. The usual recommended dose in adult cattle and horses is 500 to 3000 mL, depending on size and condition.

STORAGE AND HANDLING

Store at controlled room temperature between 15o and 30oC (59o-86oF).

TAKE TIME OBSERVE LABEL DIRECTIONS

Composition

Each 100 mL of aqueous solution contains:

dextrose•H2O ....................................... 5 g

sodium acetate•3H2O ..................... 250 mg

magnesium sulfate•7H2O .................. 20 mg

potassium chloride ........................... 20 mg

calcium chloride•2H2O ..................... 15 mg

Comprised of: niacinamide, pyridoxine HCl, thiamine HCl, d-Panthenol, Riboflavin, Cyanocobalamin (B12), l-argenine HCl, l-cysteine HCl H2O, l-glutamic acid, l-histidine HCl H2O, l-isoleucie, l-leucine, l-lycine HCl, l-methionine, l-phenylalamine, l-theonine, l-valine with methylparaben 0.18%, ethylparaben 0.01%, propylparaben 0.02%.